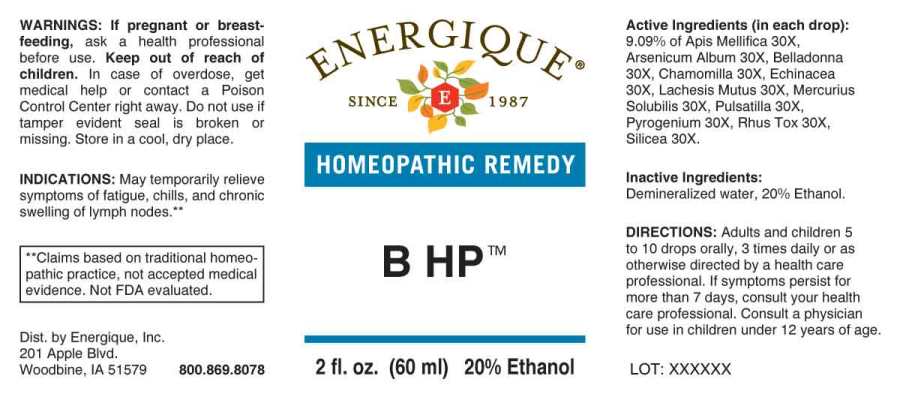 DRUG LABEL: B HP
NDC: 44911-0620 | Form: LIQUID
Manufacturer: Energique, Inc.
Category: homeopathic | Type: HUMAN OTC DRUG LABEL
Date: 20240508

ACTIVE INGREDIENTS: APIS MELLIFERA 30 [hp_X]/1 mL; ARSENIC TRIOXIDE 30 [hp_X]/1 mL; ATROPA BELLADONNA 30 [hp_X]/1 mL; MATRICARIA CHAMOMILLA WHOLE 30 [hp_X]/1 mL; ECHINACEA ANGUSTIFOLIA WHOLE 30 [hp_X]/1 mL; LACHESIS MUTA VENOM 30 [hp_X]/1 mL; MERCURIUS SOLUBILIS 30 [hp_X]/1 mL; PULSATILLA VULGARIS WHOLE 30 [hp_X]/1 mL; RANCID BEEF 30 [hp_X]/1 mL; TOXICODENDRON PUBESCENS LEAF 30 [hp_X]/1 mL; SILICON DIOXIDE 30 [hp_X]/1 mL
INACTIVE INGREDIENTS: WATER; ALCOHOL

DRUG FACTS:

ACTIVE INGREDIENTS:

(in each drop): 9.09% of Apis Mellifica 30X, Arsenicum Album 30X, Belladonna 30X, Chamomilla 30X, Echinacea (Angustifolia) 30X, Lachesis Mutus 30X, Mercurius Solubilis 30X, Pulsatilla (Vulgaris) 30X, Pyrogenium 30X, Rhus Tox 30X, Silicea 30X.

INDICATIONS:

May temporarily relieve symptoms of fatigue, chills, and chronic swelling of lymph nodes. **

**Claims based on traditional homeopathic practice, not accepted medical evidence. Not FDA evaluated.

WARNINGS:

If pregnant or breast-feeding, ask a health professional before use.

Keep out of reach of children. In case of overdose, get medical help or contact a Poison Control Center right away.

Do not use if tamper evident seal is broken or missing. Store in a cool, dry place.

Keep out of reach of children. In case of overdose, get medical help or contact a Poison Control Center right away.

DIRECTIONS:

Adults and children 5 to 10 drops orally, 3 times daily or as otherwise directed by a health care professional. If symptoms persist for more than 7 days, consult your health care professional. Consult a physician for use in children under 12 years of age.

INDICATIONS:

May temporarily relieve symptoms of fatigue, chills, and chronic swelling of lymph nodes. **

**Claims based on traditional homeopathic practice, not accepted medical evidence. Not FDA evaluated.

INACTIVE INGREDIENTS:

Demineralized water, 20% Ethanol.

QUESTIONS:

Dist. by Energique, Inc.

201 Apple Blvd.

Woodbine, IA 51579

800-869-8078

PACKAGE LABEL DISPLAY:

ENERGIQUE

SINCE 1987

HOMEOPATHIC REMEDY

B HP

2 fl. oz. (60 ml)